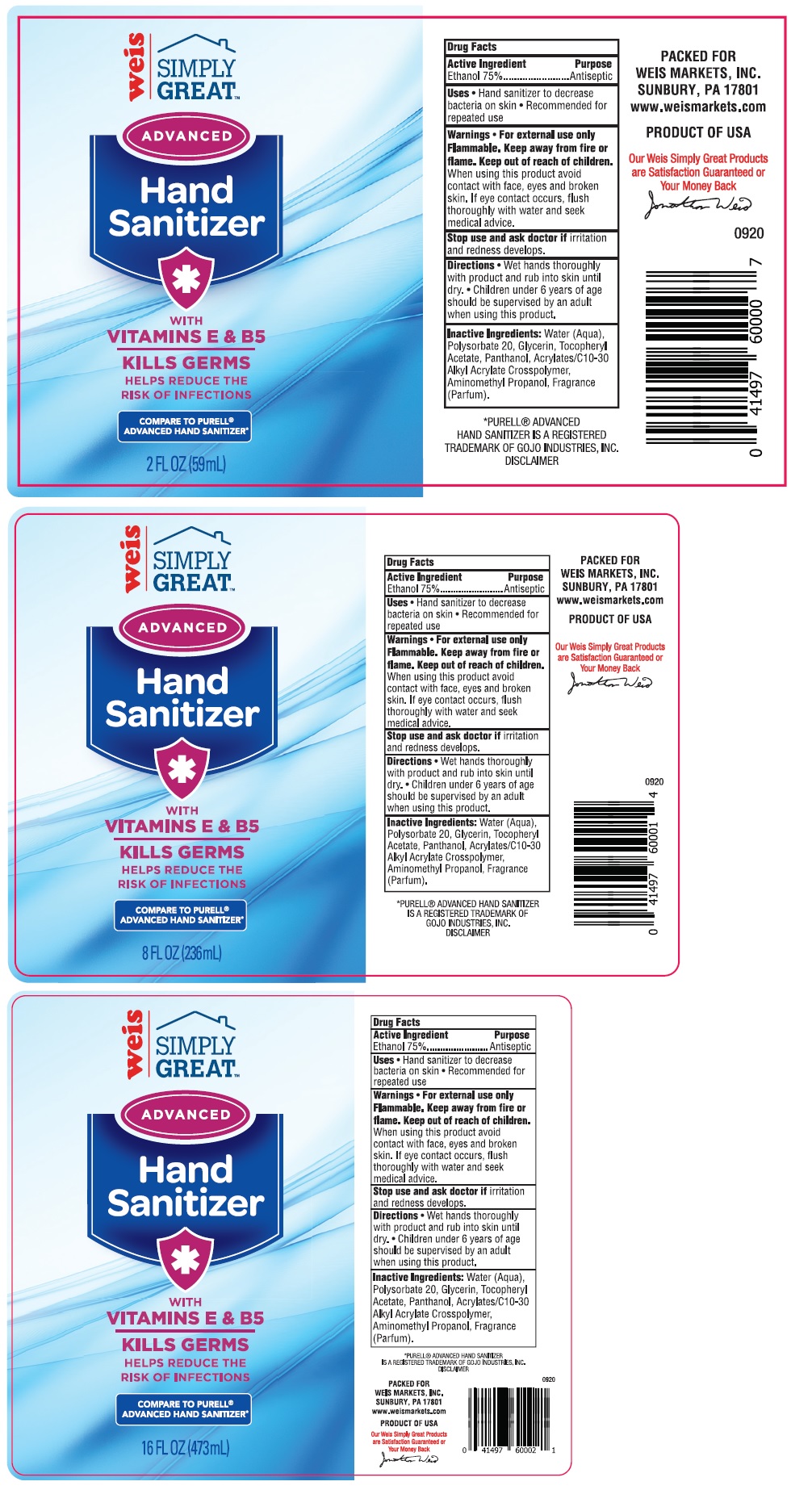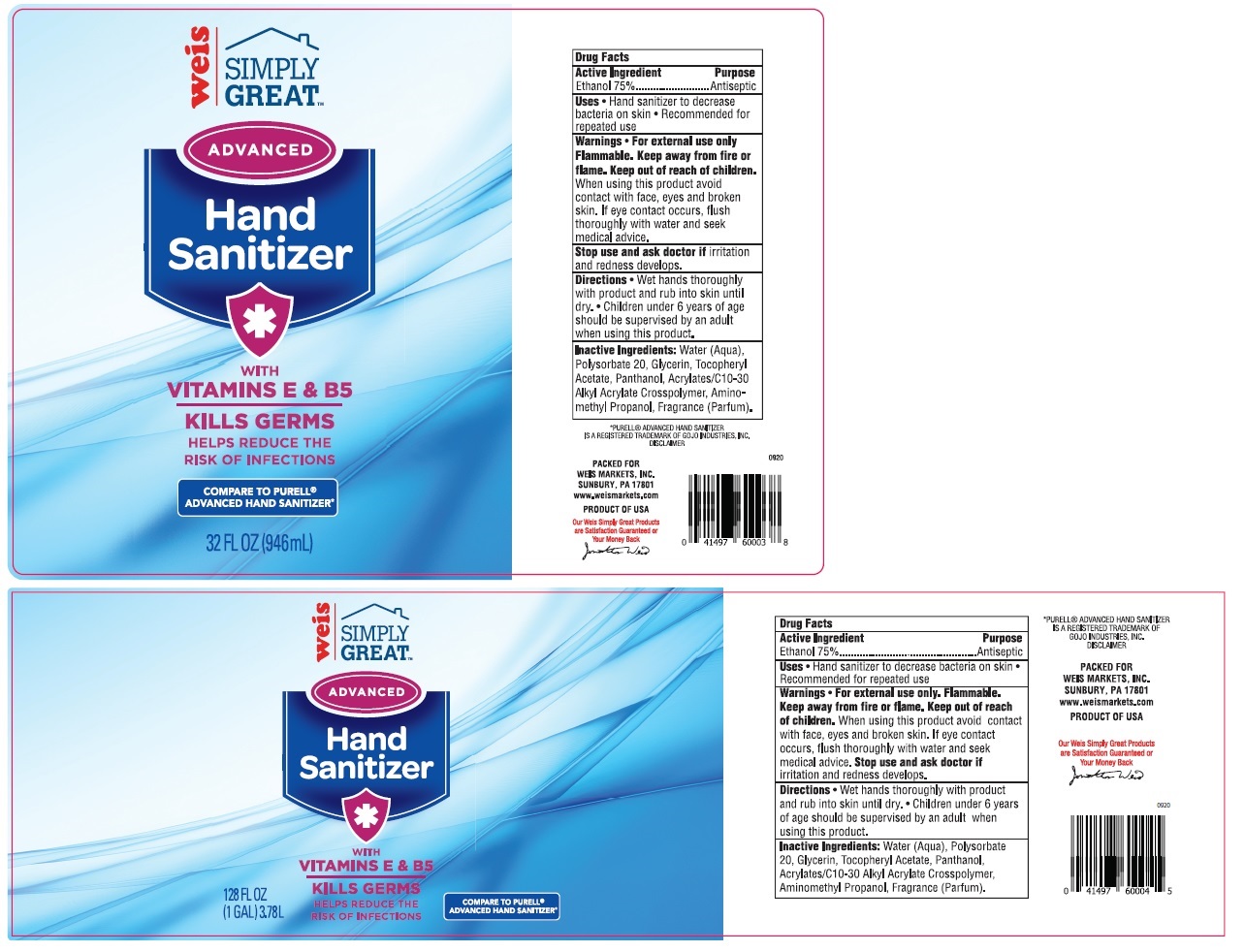 DRUG LABEL: Weis SIMPLY GREAT ADVANCED Hand Sanitizer WITH VITAMINS E and B5
NDC: 72956-100 | Form: GEL
Manufacturer: Weis Markets, Inc.
Category: otc | Type: HUMAN OTC DRUG LABEL
Date: 20230202

ACTIVE INGREDIENTS: ALCOHOL 75 mL/100 mL
INACTIVE INGREDIENTS: WATER; POLYSORBATE 20; GLYCERIN; .ALPHA.-TOCOPHEROL ACETATE; PANTHENOL; CARBOMER INTERPOLYMER TYPE A (ALLYL SUCROSE CROSSLINKED); AMINOMETHYLPROPANOL

Weis SIMPLY GREATTM ADVANCED Hand Sanitizer WITH VITAMINS E & B5

Active Ingredient

Ethanol 75%

Purpose

Antiseptic

Uses

• Hand sanitizer to decrease bacteria on skin • Recommended for repeated use

Warnings

• For external use only

Flammable. Keep away from fire or flame.

When using this product avoid contact with face, eyes and broken skin. If eye contact occurs, flush thoroughly with water and seek medical advice.

Stop use and ask doctor if irritation and redness develops.

Keep out of reach of children.

Directions

• Wet hands thoroughly with product and rub into skin until dry. • Children under 6 years of age should be supervised by an adult when using this product.

Inactive Ingredients:

Water (Aqua), Polysorbate 20, Glycerin, Tocopheryl Acetate, Panthenol, Acrylates/C10-30 Alkyl Acrylate Crosspolymer, Aminomethyl Propanol, Fragrance (Parfum).

KILLS GERMS

HELPS REDUCE THE RISK OF INFECTIONS

COMPARE TO PURELL® ADVANCED HAND SANITIZER*

*PURELL® ADVANCED HAND SANITIZER IS A REGISTERED TRADEMARK OF GOJO INDUSTRIES, INC. DISCLAIMER

PACKED FOR
WEIS MARKETS, INC.
SUNBURY, PA 17801
www.weismarkets.com

PRODUCT OF USA

Our Weis Simply Great Products are Satisfaction Guaranteed or Your Money Back